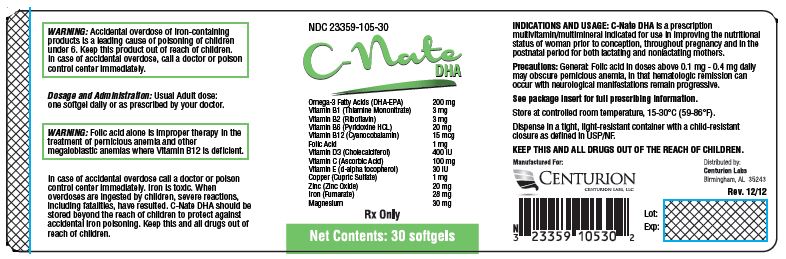 DRUG LABEL: C-Nate DHA
NDC: 23359-105 | Form: CAPSULE, GELATIN COATED
Manufacturer: Centurion Labs, LLC
Category: prescription | Type: HUMAN PRESCRIPTION DRUG LABEL
Date: 20240122

ACTIVE INGREDIENTS: OMEGA-3 FATTY ACIDS 200 mg/1 1; THIAMINE MONONITRATE 3 mg/1 1; RIBOFLAVIN 3 mg/1 1; PYRIDOXINE HYDROCHLORIDE 20 mg/1 1; CYANOCOBALAMIN 15 ug/1 1; FOLIC ACID 1 mg/1 1; CHOLECALCIFEROL 400 [iU]/1 1; ASCORBIC ACID 100 mg/1 1; .ALPHA.-TOCOPHEROL, D- 30 [iU]/1 1; CUPRIC SULFATE 1 mg/1 1; ZINC OXIDE 20 mg/1 1; FERROUS FUMARATE 28 mg/1 1; MAGNESIUM 30 mg/1 1
INACTIVE INGREDIENTS: GELATIN; GLYCERIN; YELLOW WAX; LECITHIN, SOYBEAN; WATER

C-Nate DHA

PRENATAL / MULTIVITAMIN

Rev. 10/12

Rx ONLY

DESCRIPTION

Each Softgel Contains:
Omega-3 Fatty Acids (DHA-EPA) | 200mg
Vitamin B1 (Thiamine Mononitrate) | 3 mg
Vitamin B2 (Riboflavin) | 3 mg
Vitamin B6 (Pyridoxine HCL) | 20 mg
Vitamin B12 (Cyanocobalamin) | 15 mcg
Folic Acid | 1 mg
Vitamin D3 (Cholecalciferol) | 400 IU
Vitamin C (Ascorbic Acid) | 100 mg
Vitamin E (d-alpha tocopherol) | 30 IU
Copper (Cupric Sulfate) | 1 mg
Zinc (Zinc Oxide) | 20 mg
Iron (Fumerate) | 28 mg
Magnesium | 30 mg

INACTIVE INGREDIENT

INACTIVE INGREDIENTS: Gelatin, Glycerol, beeswax yellow, lecithin, water-purified and colorant.

INDICATIONS AND USAGE: C-NATE DHA is a prescription multivitamin/multimineral indicated for use in improving the nutritional status of women prior to conception, throughout pregnancy and in the postnatal period for both lactating and nonlactating mothers.

CONTRAINDICATIONS

CONTRAINDICATIONS: C-NATE DHA should not be used by patients with known history of hypersensitivity to any of the listed ingredients.

PRECAUTIONS

PRECAUTIONS: Folic Acid alone is improper therapy in the treatment of pernicious anemia and other megaloblastic anemias where vitamin B12 is deficient. Folic Acid in doses above 0.1 mg daily may obscure pernicious anemia in that hematologic remission can occur while neurological manifestations progress. Allergic sensitization has been reported following both oral and parenteral administration of folic acid.

WARNINGS

WARNING: Accidental overdose of iron-containing products is a leading cause of fatal poisoning in children under 6. KEEP THIS PRODUCT OUT OF REACH OF CHILDREN. In case of accidental overdose, call a doctor or poison control center immediately.

PEDIATRIC USE

PEDIATRIC USE: Safety and effectiveness in pediactric patients has not been established.

GERIATRIC USE

GERIACTRIC USE: No clinical studies have been performed in patients over 65 to determine whether older persons respond differently from younger persons. Physicians should consider that elderly person may have decreased hepatic, renal, or cardiac function.

DRUG INTERACTIONS

DRUG INTERACTIONS: C-NATE DHA softgels are not recommended for and should not be given to patients receiving levodopa because the action of levodopa is antagonized by pyridoxine.

ADVERSE REACTIONS

ADVERSE REACTIONS: Adverse reactions have been reported with specific vitamins and minerals but generally at levels substantially higher than those contained herein. However, allergic and idiosyncratic reactions are possible at lower levels. Iron, even at the usual recommended levels, has been associated with gastrointestinal intolerance in some patients.

DOSAGE AND ADMINISTRATION: Usual adult dose: one softgel daily or as prescribed by your doctor.

HOW SUPPLIED

HOW SUPPLIED: C-NATE DHA is available as a Annato colored softgel, imprinted PRE 01. Available in 30 count bottles with NDC #23359-105-30 and samples with NDC #23359-105-05 and NDC #23359-105-01.

PHYSICIAN SAMPLE NOT FOR RESALE

STORAGE AND HANDLING

Recommended Storage: 15°-30°C (59°-86°F) degrees. Protect from light moisture and avoid excessive heat. Dispense original carton.

KEEP OUT OF REACH OF CHILDREN

RX ONLY

CENTURION LABS, LLC
BIRMINGHAM, AL 35243

PACKAGE LABEL.PRINCIPAL DISPLAY PANEL

NDC 23359-105-30

C-Nate
DHA

Softgels
Omega-3 Fatty Acids (DHA-EPA) | 200mg
Vitamin B1 (Thiamine Mononitrate) | 3 mg
Vitamin B2 (Riboflavin) | 3 mg
Vitamin B6 (Pyridoxine HCL) | 20 mg
Vitamin B12 (Cyanocobalamin) | 15 mcg
Folic Acid | 1 mg
Vitamin D3 (Cholecalciferol) | 400 IU
Vitamin C (Ascorbic Acid) | 100 mg
Vitamin E (d-alpha tocopherol) | 30 IU
Copper (Cupric Sulfate) | 1 mg
Zinc (Zinc Oxide) | 20 mg
Iron (Fumerate) | 28 mg
Magnesium | 30 mg

Rx Only

Net Contents: 30 softgels

Manufactured For:
Centurion Labs LLC

Distributed by:
Centurion Labs LLC
Birmingham, AL 35243